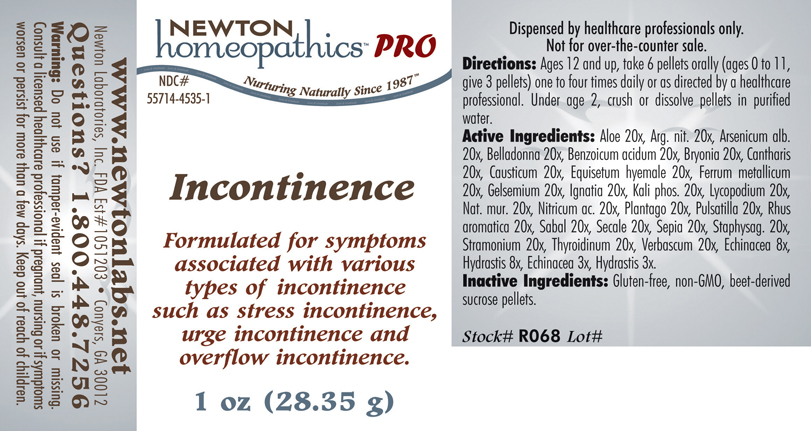 DRUG LABEL: Incontinence 
NDC: 55714-4535 | Form: PELLET
Manufacturer: Newton Laboratories, Inc.
Category: homeopathic | Type: HUMAN PRESCRIPTION DRUG LABEL
Date: 20110601

ACTIVE INGREDIENTS: Aloe 20 [hp_X]/1 g; Silver Nitrate 20 [hp_X]/1 g; Arsenic Trioxide 20 [hp_X]/1 g; Atropa Belladonna 20 [hp_X]/1 g; Benzoic Acid 20 [hp_X]/1 g; Bryonia Alba Root 20 [hp_X]/1 g; Lytta Vesicatoria 20 [hp_X]/1 g; Causticum 20 [hp_X]/1 g; Equisetum Hyemale 20 [hp_X]/1 g; Iron 20 [hp_X]/1 g; Gelsemium Sempervirens Root 20 [hp_X]/1 g; Strychnos Ignatii Seed 20 [hp_X]/1 g; Potassium Phosphate, Dibasic 20 [hp_X]/1 g; Lycopodium Clavatum Spore 20 [hp_X]/1 g; Sodium Chloride 20 [hp_X]/1 g; Nitric Acid 20 [hp_X]/1 g; Plantago Major 20 [hp_X]/1 g; Pulsatilla Vulgaris 20 [hp_X]/1 g; Rhus Aromatica Root Bark 20 [hp_X]/1 g; Saw Palmetto 20 [hp_X]/1 g; Claviceps Purpurea Sclerotium 20 [hp_X]/1 g; Sepia Officinalis Juice 20 [hp_X]/1 g; Delphinium Staphisagria Seed 20 [hp_X]/1 g; Datura Stramonium 20 [hp_X]/1 g; Thyroid, Unspecified 20 [hp_X]/1 g; Verbascum Thapsus 20 [hp_X]/1 g; Echinacea, Unspecified 8 [hp_X]/1 g; Goldenseal 8 [hp_X]/1 g
INACTIVE INGREDIENTS: Sucrose

Incontinence

INDICATIONS & USAGE SECTION

Incontinence Formulated for symptoms associated with various types of incontinence such as stress incontinence, urge incontinence and overflow incontinence.

DOSAGE & ADMINISTRATION SECTION

Directions: Ages 12 and up, take 6 pellets orally (ages 0 to 11, give 3 pellets) one to four times daily or as directed by a healthcare professional. Under age 2, crush or dissolve pellets in purified water.

ACTIVE INGREDIENT SECTION

Aloe 20x, Arg. nit. 20x, Arsenicum alb. 20x, Belladonna 20x, Benzoicum acidum 20x, Bryonia 20x, Cantharis 20x, Causticum 20x, Equisetum hyemale 20x, Ferrum metallicum 20x, Gelsemium 20x, Ignatia 20x, Kali phos. 20x, Lycopodium 20x, Nat. mur. 20x, Nitricum ac. 20x, Plantago 20x, Pulsatilla 20x, Rhus aromatica 20x, Sabal 20x, Secale 20x, Sepia 20x, Staphysag. 20x, Stramonium 20x, Thyroidinum 20x, Verbascum 20x, Echinacea 8x, Hydrastis 8x, Echinacea 3x, Hydrastis 3x.

PURPOSE SECTION

Formulated for symptoms associated with various types of incontinence such as stress incontinence, urge incontinence and overflow incontinence.

INACTIVE INGREDIENT SECTION

Inactive Ingredients: Gluten-free, non-GMO, beet-derived sucrose pellets.

QUESTIONS? SECTION

www.newtonlabs.net Newton Laboratories, Inc. FDA Est # 1051203 - Conyers, GA 30012
Questions? 1.800.448.7256

WARNINGS SECTION

Warning: Do not use if tamper - evident seal is broken or missing. Consult a licensed healthcare professional if pregnant, nursing or if symptoms worsen or persist for more than a few days. Keep out of reach of children.

PREGNANCY OR BREAST FEEDING SECTION

Consult a licensed healthcare professional if pregnant or nursing or if symptoms worsen or persist for more than a few days.

KEEP OUT OF REACH OF CHILDREN SECTION

Keep out of reach of children.